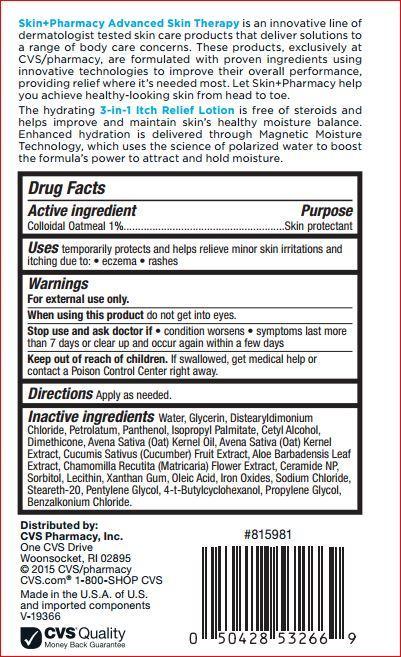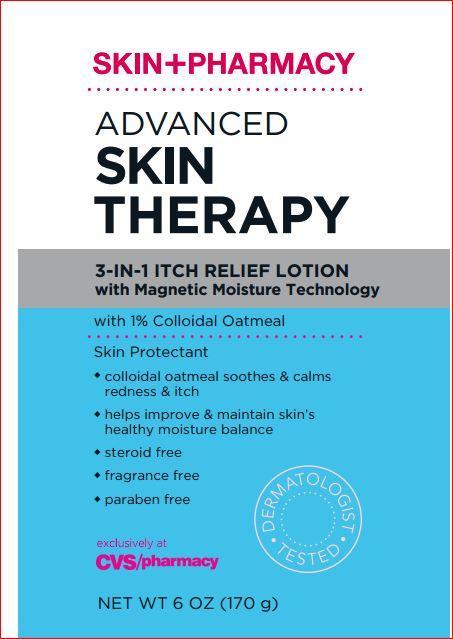 DRUG LABEL: 3-In-1 Relief
NDC: 59779-451 | Form: LOTION
Manufacturer: CVS
Category: otc | Type: HUMAN OTC DRUG LABEL
Date: 20171208

ACTIVE INGREDIENTS: OATMEAL 1.0 g/100 g
INACTIVE INGREDIENTS: Water; Glycerin; Distearyldimonium Chloride; Petrolatum; Panthenol; Isopropyl Palmitate; Cetyl Alcohol; OAT KERNEL OIL; OAT; Dimethicone; Cucumber; ALOE VERA LEAF; CHAMOMILE; CERAMIDE NP; Sorbitol; Xanthan Gum; Oleic Acid; FERROUS OXIDE; Sodium Chloride; Steareth-20; Pentylene Glycol; 4-TERT-BUTYLCYCLOHEXANOL; Propylene Glycol; Benzalkonium Chloride

Drug Facts

Active ingredient Purpose

Colloidal Oatmeal - 1.00%.................................Skin Protectant

Uses

temporarily protects and helps relieve minor skin irritations and itching due to: • eczema • rashes

Warning

For external use only.

When using this product • do not get into eyes.

Stop use and ask a doctor if • condition worsens • symptoms persist for more than 7 days or clear up and occur again within a few days

Keep out of reach of children. If swallowed, get medical help or contact a Poison Control Center immediately.

DOSAGE AND ADMINISTRATION

Directions • Apply as needed

Inactive ingredients

Water, Glycerin, Distearyldimonium Chloride, Petrolatum, Panthenol, Isopropyl Palmitate, Cetyl Alcohol, Dimethicone, Avena Sativa (Oat) , Kernel Oil, Avena Sativa (Oat) Kernel Extract, Cucumis Sativus (Cucumber) Fruit Extract, Aloe Barbadensis Leaf Extract, Chamomilla Recutita , Matricaria) Flower Extract, Ceramide NP, Sorbitol, Lecithin, Xanthan Gum, Oleic Acid, Iron Oxides, Sodium Chloride, Steareth-20, Pentylene , Glycol, 4-t-Butylcyclohexanol, Propylene Glycol, Benzalkonium Chloride